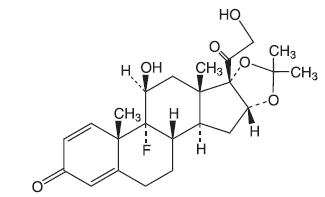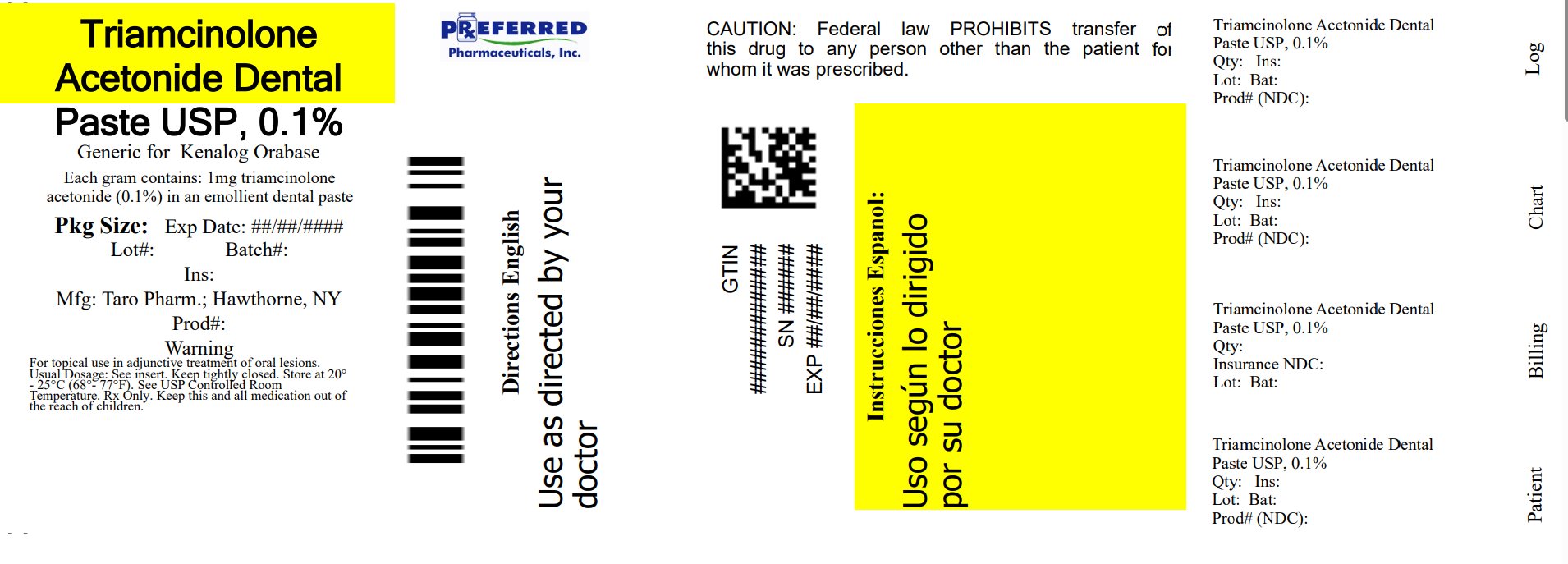 DRUG LABEL: Triamcinolone Acetonide
NDC: 68788-7814 | Form: PASTE
Manufacturer: Preferred Pharmaceuticals Inc
Category: prescription | Type: HUMAN PRESCRIPTION DRUG LABEL
Date: 20251001

ACTIVE INGREDIENTS: Triamcinolone Acetonide 1 mg/1 g
INACTIVE INGREDIENTS: GELATIN, UNSPECIFIED; pectin; CARBOXYMETHYLCELLULOSE SODIUM, UNSPECIFIED; POLYETHYLENE GLYCOL, UNSPECIFIED; mineral oil

Triamcinolone Acetonide
Dental Paste USP, 0.1%

Rx only

DESCRIPTION

Triamcinolone Acetonide Dental Paste USP, 0.1%, contains the corticosteroid triamcinolone acetonide in an adhesive vehicle suitable for application to oral tissues. Triamcinolone acetonide is designated chemically as 9-fluoro-11β, 16α, 17, 21-tetrahydroxypregna-1, 4-diene-3, 20-dione cyclic 16, 17-acetal with acetone. The structural formula of triamcinolone acetonide is as follows:

C 24H 31FO 6 MW 434.50

Each gram of triamcinolone acetonide dental paste contains 1 mg triamcinolone acetonide in an emollient dental paste containing carboxymethylcellulose sodium, gelatin, and pectin in a plasticized hydrocarbon gel (a polyethylene and mineral oil gel base).

CLINICAL PHARMACOLOGY

Like other topical corticosteroids, triamcinolone acetonide has anti-inflammatory, antipruritic, and vasoconstrictive properties. The mechanism of the anti-inflammatory activity of the topical steroids, in general, is unclear. However, corticosteroids are thought to act by the induction of phospholipase A 2inhibitory proteins, collectively called lipocortins. It is postulated that these proteins control the biosynthesis of potent mediators of inflammation such as prostaglandins and leukotrienes by inhibiting the release of their common precursor, arachidonic acid. Arachidonic acid is released from membrane phospholipids by phospholipase A 2.

Pharmacokinetics

The extent of absorption through the oral mucosa is determined by multiple factors including the vehicle, the integrity of the mucosal barrier, the duration of therapy, and the presence of inflammation and/or other disease processes. Once absorbed through the mucous membranes, the disposition of corticosteroids is similar to that of systemically administered corticosteroids. Corticosteroids are bound to the plasma proteins in varying degrees. Corticosteroids are metabolized primarily in the liver and are then excreted by the kidneys; some corticosteroids and their metabolites are also excreted into the bile.

INDICATIONS AND USAGE

Triamcinolone Acetonide Dental Paste USP, 0.1% is indicated for adjunctive treatment and for the temporary relief of symptoms associated with oral inflammatory lesions and ulcerative lesions resulting from trauma.

CONTRAINDICATIONS

Triamcinolone acetonide dental paste is contraindicated in those patients with a history of hypersensitivity to any of the components of the preparation; it is also contraindicated in the presence of fungal, viral, or bacterial infections of the mouth or throat.

PRECAUTIONS

General

Triamcinolone acetonide dental paste may cause local adverse reactions. If irritation develops, triamcinolone acetonide dental paste should be discontinued and appropriate therapy instituted. Allergic contact sensitization with corticosteroids is usually diagnosed by observing failure to heal rather than noting a clinical exacerbation as with most topical products not containing corticosteroids. Such an observation should be corroborated with appropriate diagnostic patch testing.

If concomitant mucosal infections are present or develop, an appropriate antifungal or antibacterial agent should be used. If a favorable response does not occur promptly, use of triamcinolone acetonide dental paste should be discontinued until the infection has been adequately controlled.

If significant regeneration or repair of oral tissues has not occurred in seven days, additional investigation into the etiology of the oral lesion is advised.

Systemic absorption of topical corticosteroids has produced reversible hypothalamic-pituitary-adrenal (HPA) axis suppression, manifestations of Cushing's syndrome, hyperglycemia, glucosuria, and other adverse effects known to occur with parenterally-administered steroid preparations; therefore, it may be advisable to periodically evaluate patients on prolonged therapy with corticosteroid-containing dental pastes for evidence of HPA axis suppression (see PRECAUTIONS, Laboratory Tests). If HPA axis suppression is noted, an attempt should be made to withdraw the drug or to reduce the frequency of application. Recovery of HPA axis function is generally prompt and complete upon discontinuation of therapy.

Information for the Patient

Patients using topical corticosteroids should receive the following information and instructions:

1. This medication is to be used as directed by the physician or dentist. It is for oral use only; it is not intended for ophthalmic or dermatological use.
2. Patients should be advised not to use this medication for any disorder other than for which it was prescribed.
3. Patients should report any signs of adverse reactions.
4. As with other corticosteroids, therapy should be discontinued when control is achieved. If no improvement is seen within 2 weeks, contact the physician or dentist.

Laboratory Tests

A urinary free cortisol test and ACTH stimulation test may be helpful in evaluating HPA axis suppression.

Carcinogenesis, Mutagenesis, Impairment of Fertility

Animal studies have not been performed to evaluate triamcinolone acetonide for potential to induce carcinogenesis, mutagenesis, or impairment of fertility.

Pregnancy Category C

Teratogenic effects

Triamcinolone acetonide has been shown to induce teratogenic effects in several species. In mice and rabbits, triamcinolone acetonide induced an increased incidence of cleft palate at dosages of approximately 120 µg/kg/day and 24 µg/kg/day, respectively (approximately 12 times and 10 times the amount in a typical daily human dose of triamcinolone acetonide dental paste when compared following normalization of the data on the basis of body surface area estimates, respectively). In monkeys, triamcinolone acetonide induced cranial skeletal malformations at the lowest dosage studied (500 µg/kg/day), which was approximately 200 times the amount in a typical daily human dose of triamcinolone acetonide dental paste when compared following normalization of the data on the basis of body surface area estimates. There are no adequate and well-controlled studies in pregnant women. However, a retrospective analysis of birth defects among children born to mothers that used drugs of the same class as triamcinolone acetonide dental paste (corticosteroids) during pregnancy found an approximately 3 times increased incidence of cleft palate. Triamcinolone acetonide dental paste should be used during pregnancy only if the potential benefit justifies the potential risk to the fetus.

Nursing Mothers

It is not known whether oral application of corticosteroids could result in sufficient systemic absorption to produce detectable quantities in breast milk. Caution should be exercised when corticosteroid-containing dental pastes are prescribed for a nursing woman.

Pediatric Use

The safety and efficacy of triamcinolone acetonide dental paste in children is unknown. Pediatric patients may demonstrate greater susceptibility to topical corticosteroid-induced HPA axis suppression and Cushing's Syndrome than mature patients because of a larger skin surface area to body weight ratio. Administration of corticosteroid-containing dental pastes to children should be limited to the least amount compatible with an effective therapeutic regimen. Chronic corticosteroid therapy may interfere with the growth and development of children.

Geriatric Use

Clinical studies of triamcinolone acetonide dental paste did not include sufficient numbers of subjects age 65 and older to determine whether they respond differently from younger subjects. Other reported clinical experience has not identified differences in responses between the elderly and younger patients.

ADVERSE REACTIONS

The following local adverse reactions may occur with corticosteroid-containing dental pastes: burning, itching, irritation, dryness, blistering or peeling not present prior to therapy, perioral dermatitis, allergic contact dermatitis, maceration of the oral mucosa, secondary infection, and atrophy of the oral mucosa.

Also, see PRECAUTIONSfor potential effects of systemic absorption.

To report SUSPECTED ADVERSE REACTINS, contact Sun Pharmaceutical Industries, Inc., at 1-866-923-4914 or FDA at 1-800-FDA-1088 or www.fda.gov/medwatch.

DOSAGE AND ADMINISTRATION

Press a small dab (about 1/4 inch) to the lesion until a thin film develops. A larger quantity may be required for coverage of some lesions. For optimal results use only enough to coat the lesion with a thin film. Do not rub in. Attempting to spread this preparation may result in granular, gritty sensation and cause it to crumble. After application, however, a smooth, slippery film develops.

The preparation should be applied at bedtime to permit steroid contact with the lesion throughout the night. Depending on the severity of symptoms, it may be necessary to apply the preparation two or three times a day, preferably after meals. If significant repair or regeneration has not occurred in seven days, further investigation is advisable.

HOW SUPPLIED

Triamcinolone Acetonide Dental Paste USP, 0.1% is supplied in tubes containing 5 g of dental paste (NDC 68788-7814-5)

Storage

Keep tightly closed. Store at 20° to 25°C (68° to 77°F)[see USP Controlled Room Temperature].

Mfd. by: Sun Pharma Canada Inc.
Brampton, Ontario, Canada L6T 1C1
Dist. by: Sun Pharmaceutical Industries, Inc.
Cranbury, NJ 08512

Revised: September 2025

5264365-0925-01 364

Relabeled By: Preferred Pharmaceuticals Inc.

PRINCIPAL DISPLAY PANEL -

NDC 68788-7814-5

Triamcinolone Acetonide
Dental Paste USP, 0.1%

FOR TOPICAL USE IN ADJUNCTIVE TREATMENT OF ORAL LESIONS

Rx only

Keep this and all medications out of the reach of children.